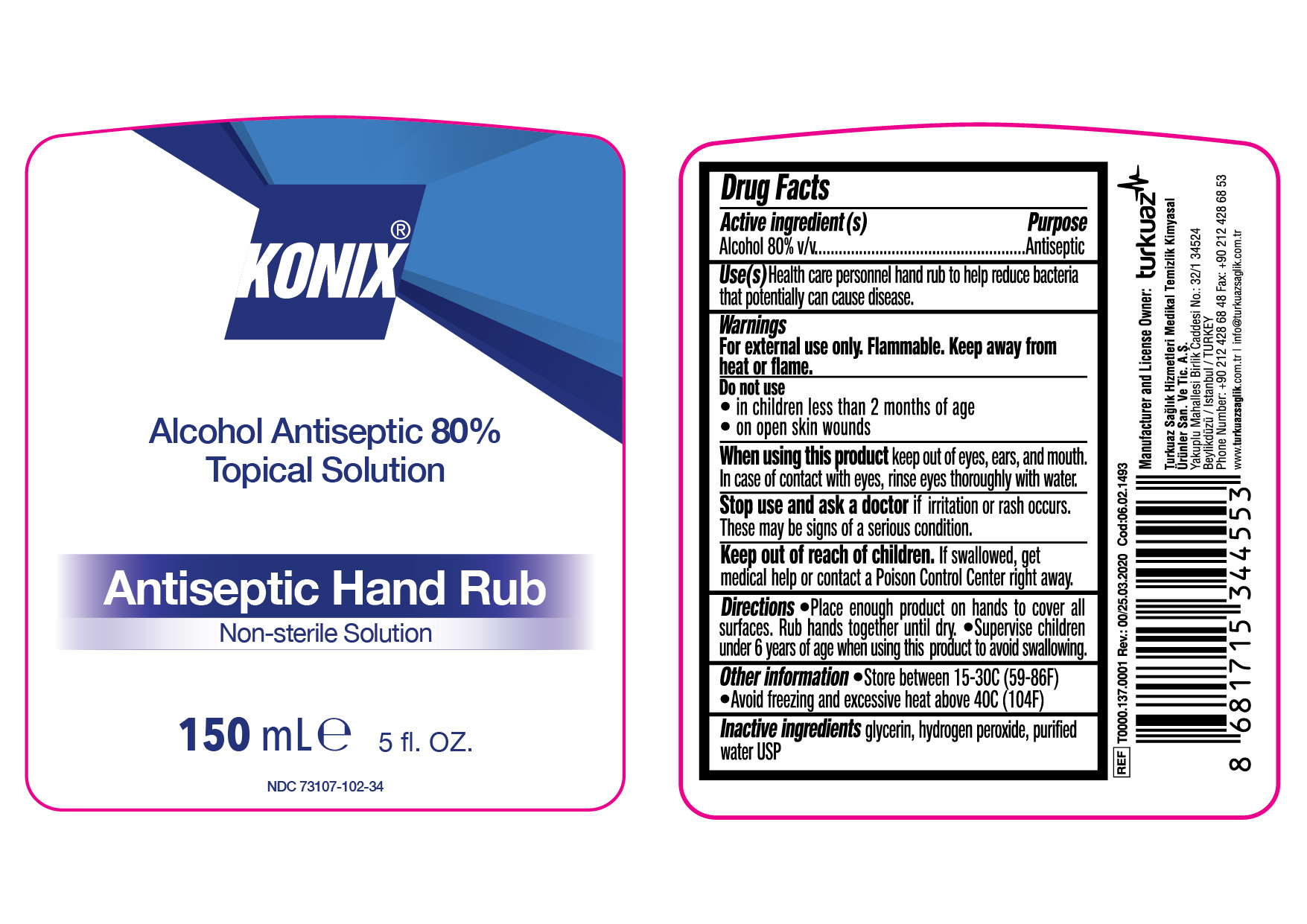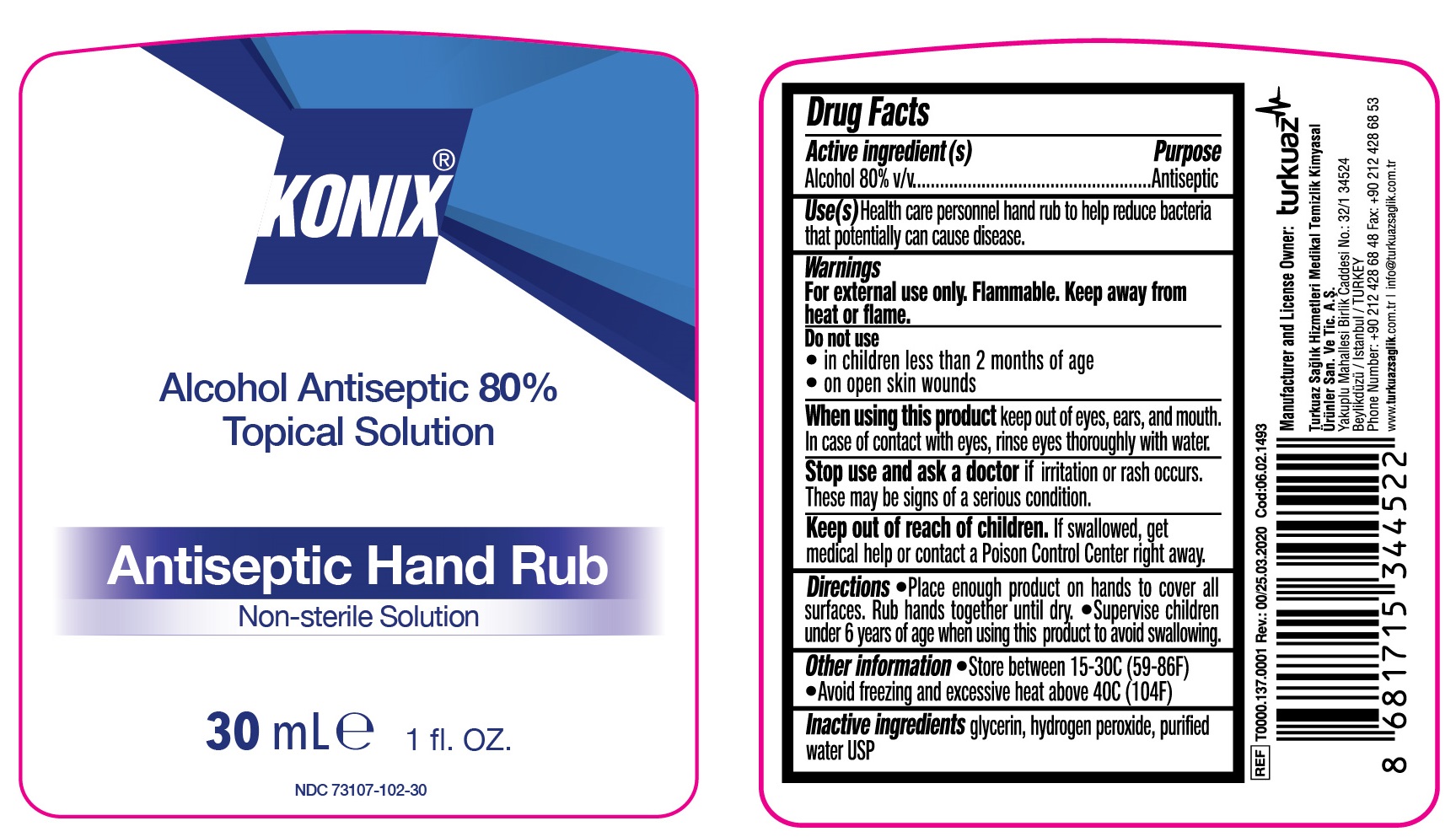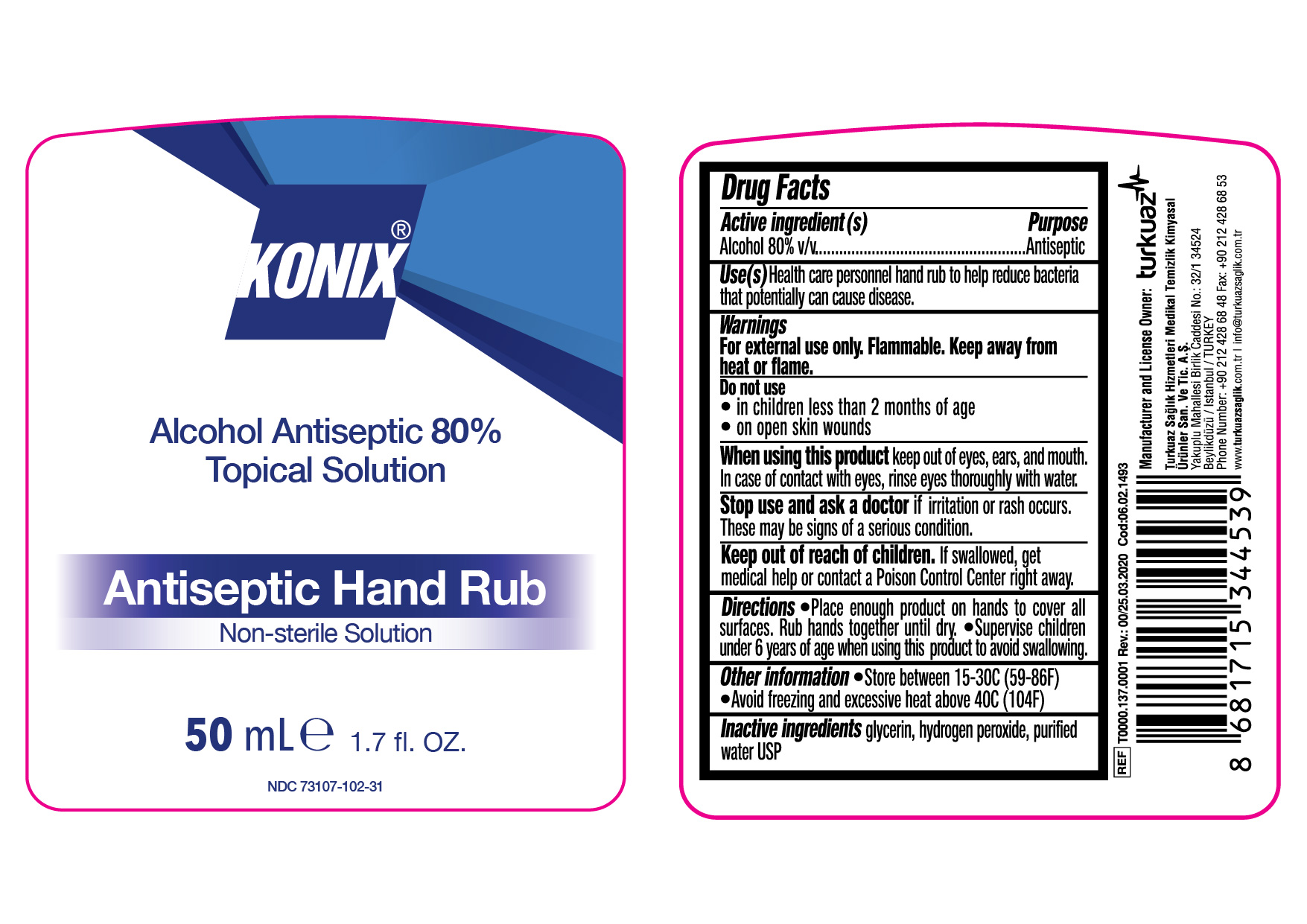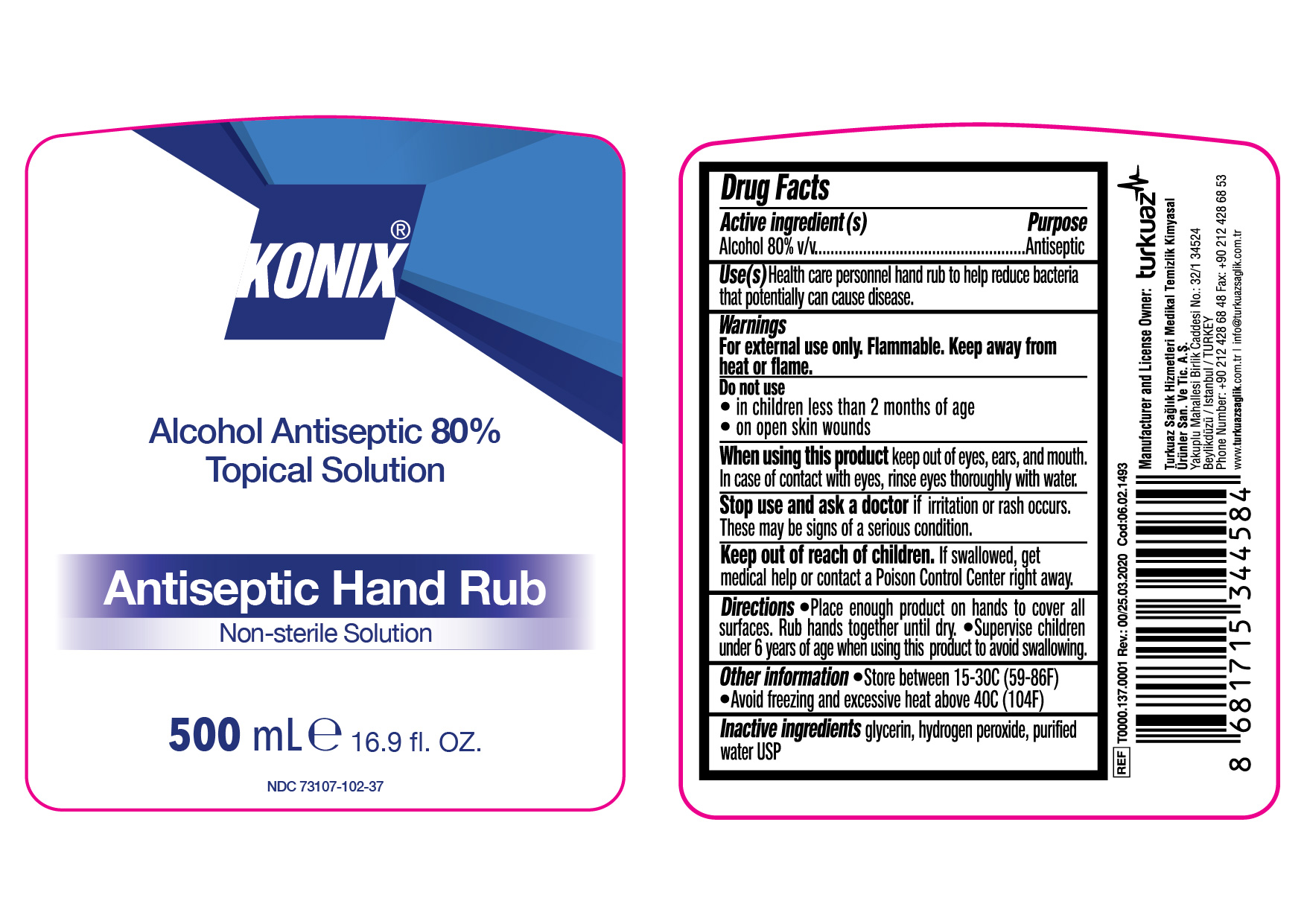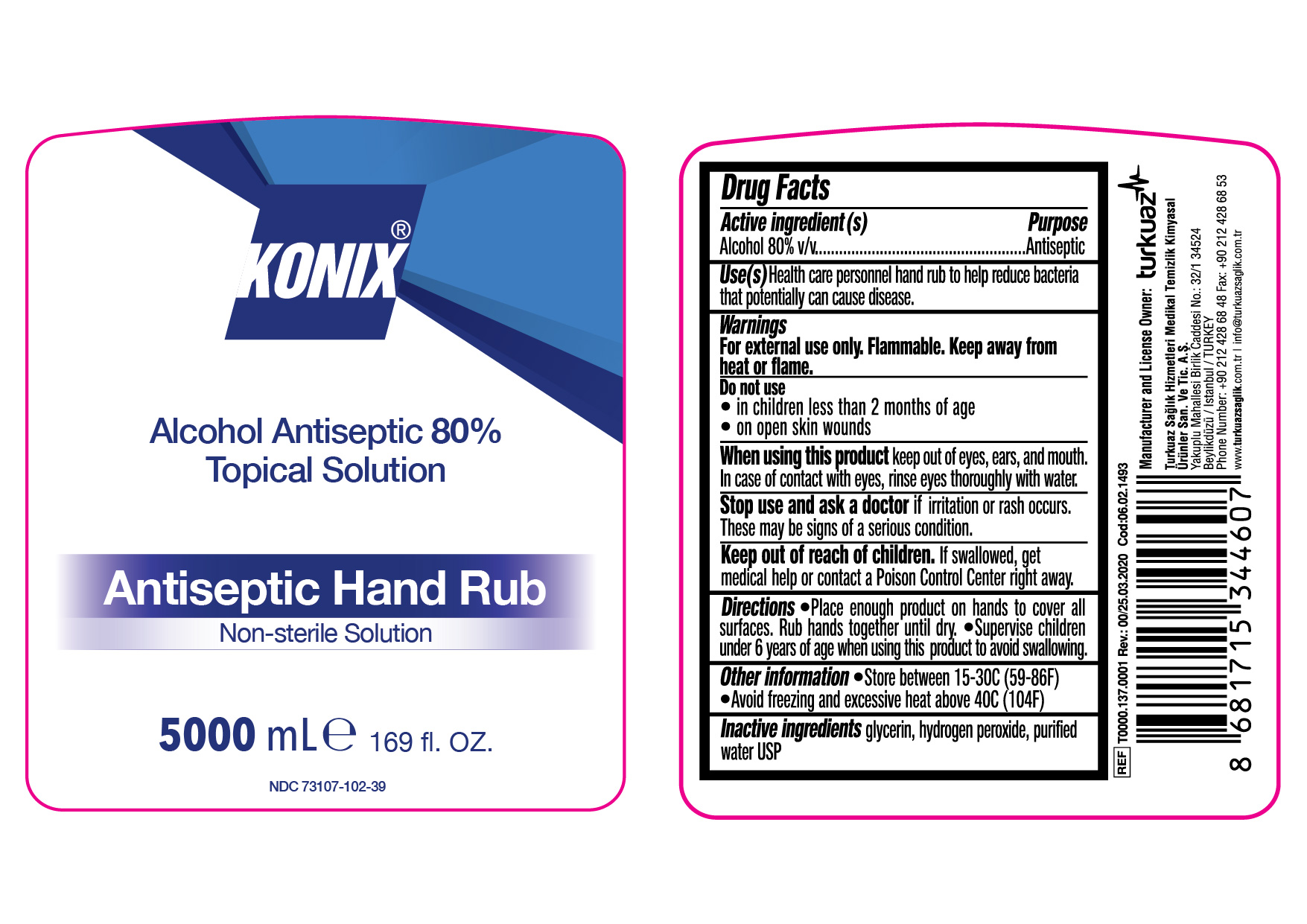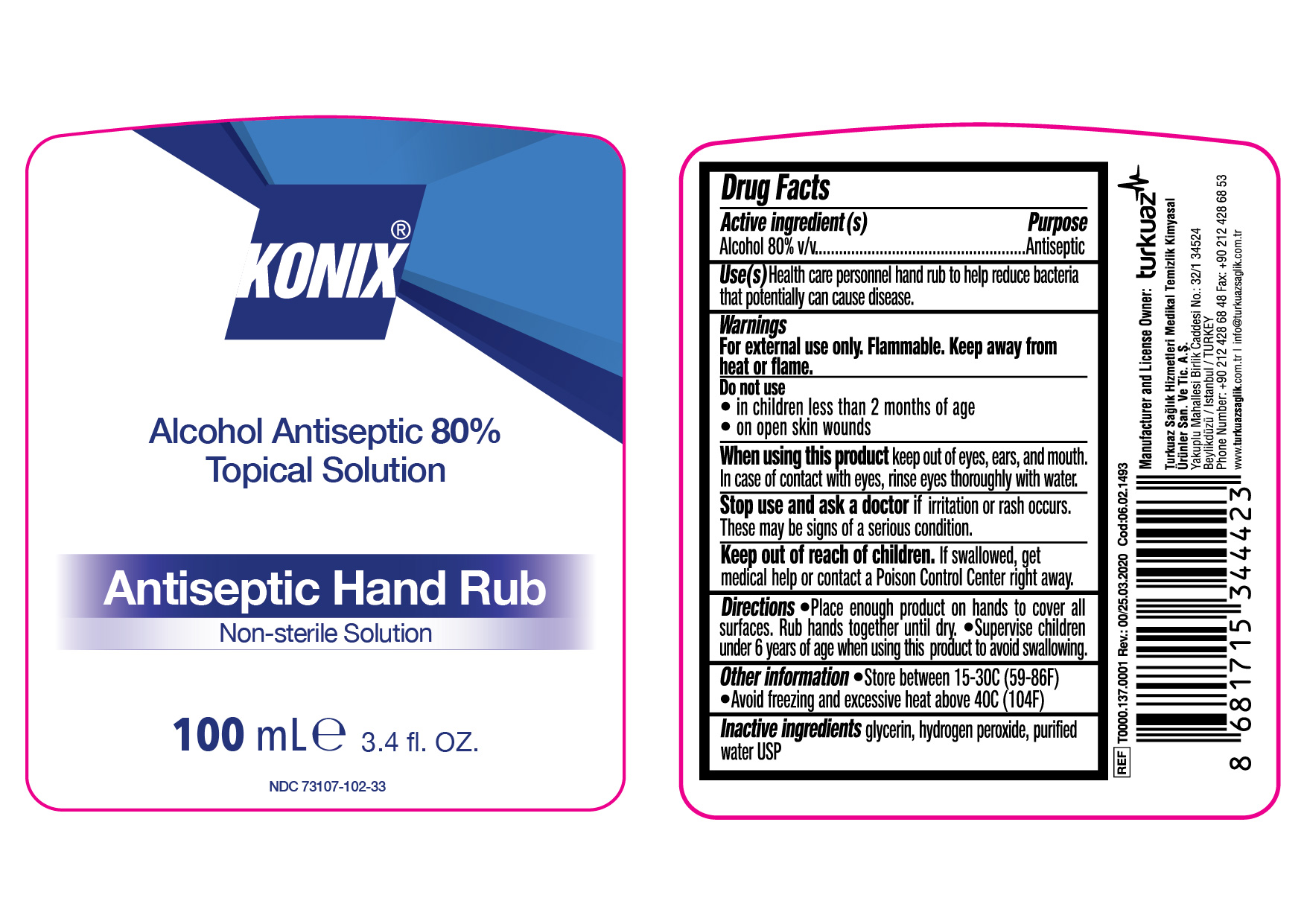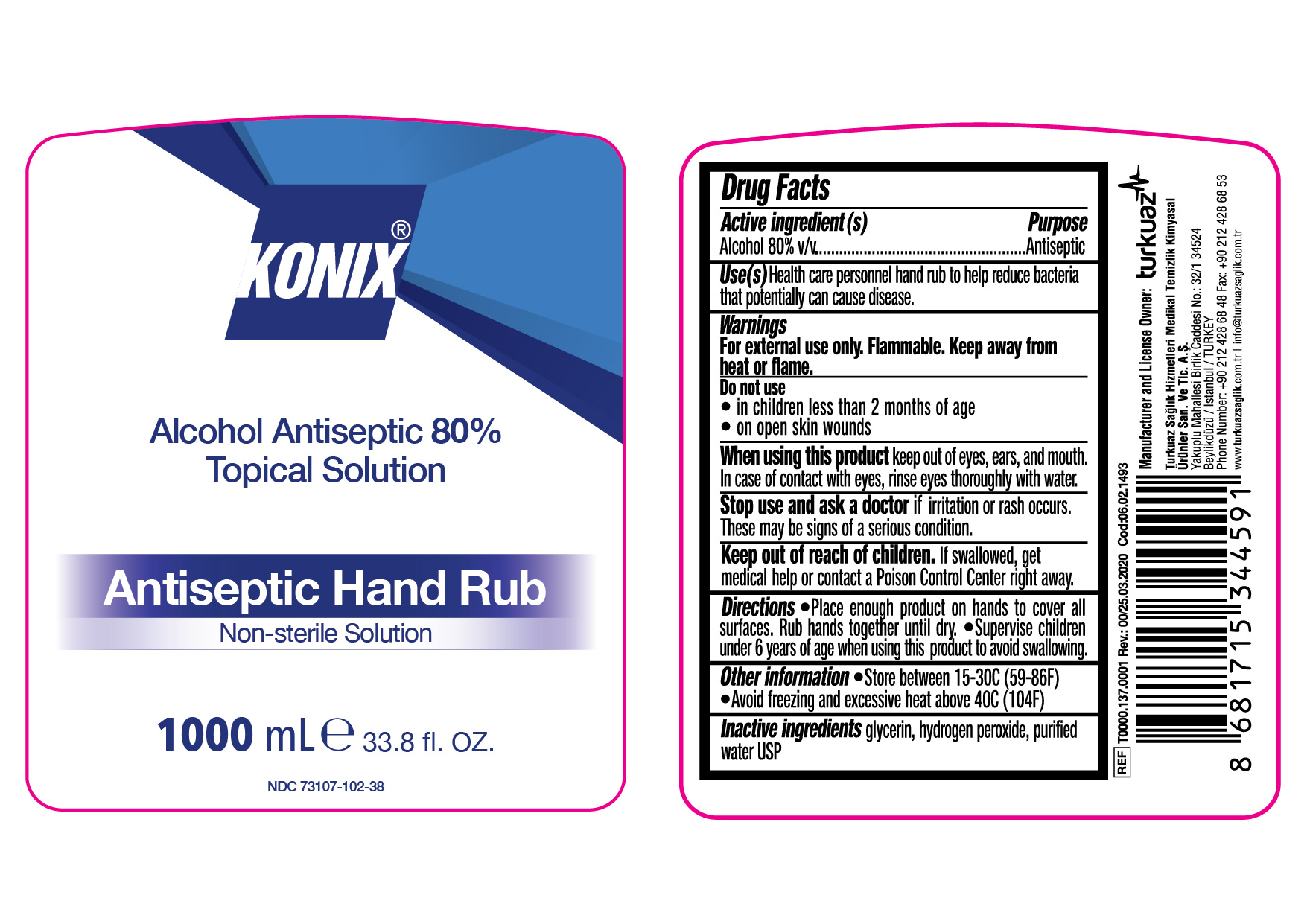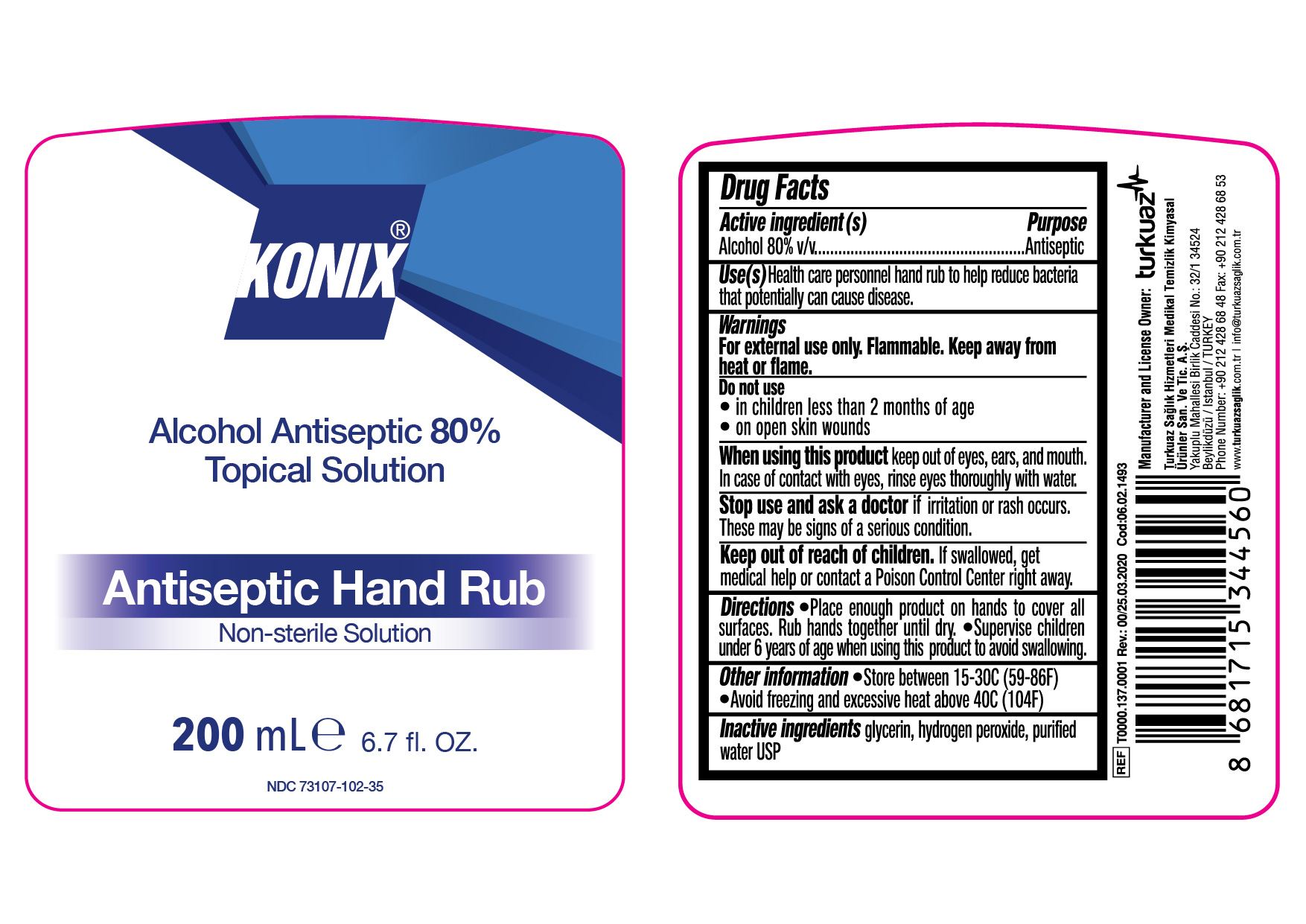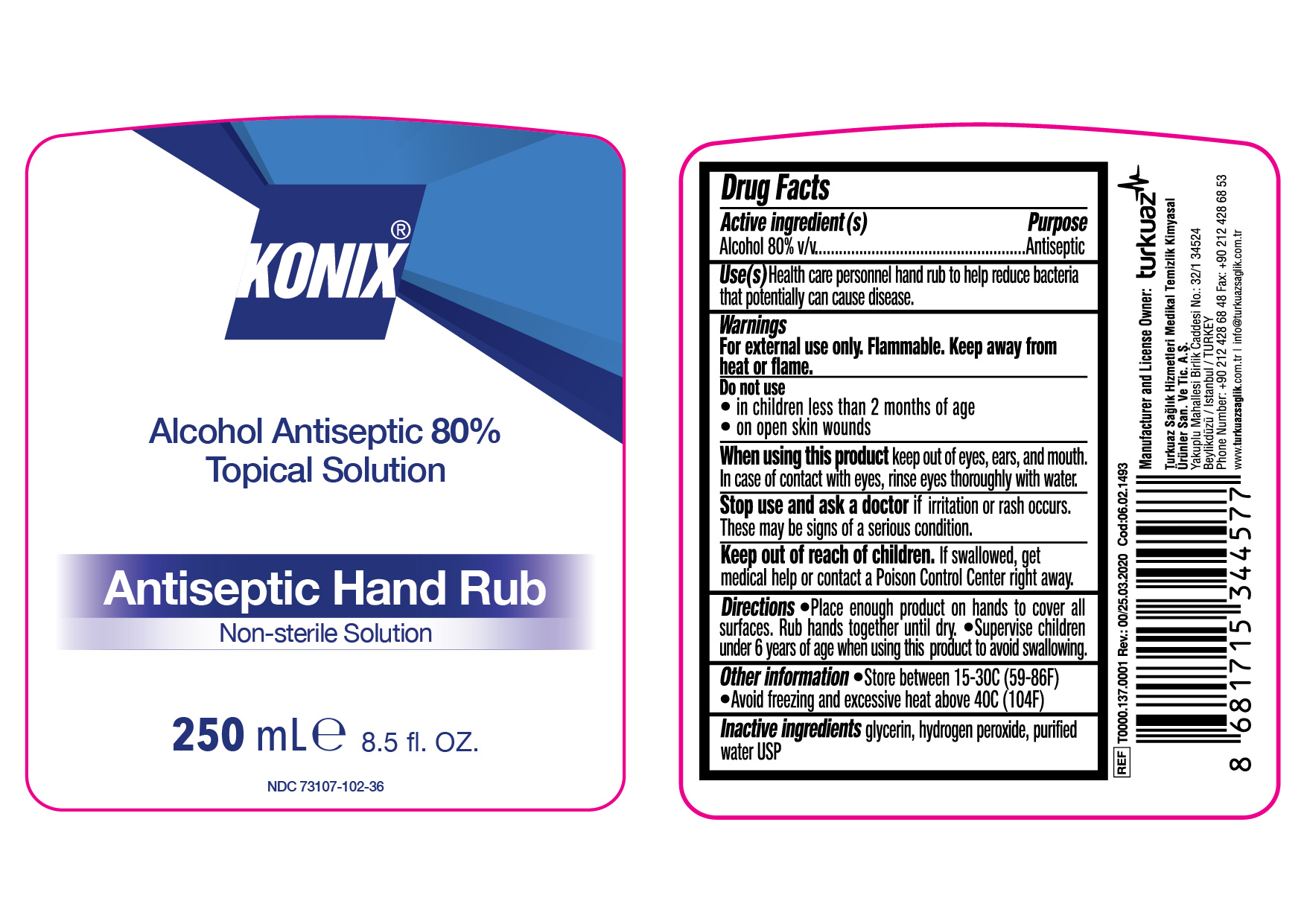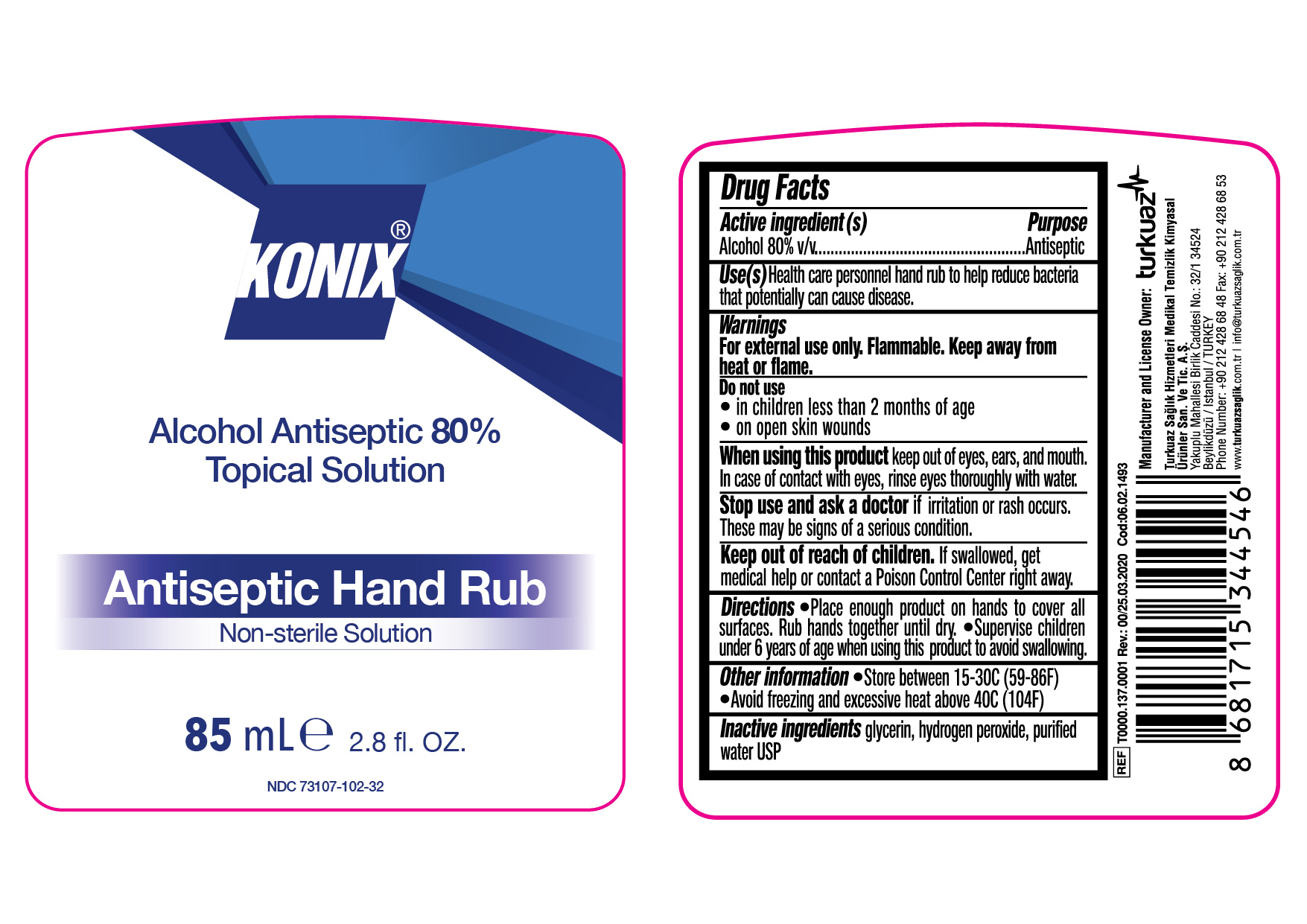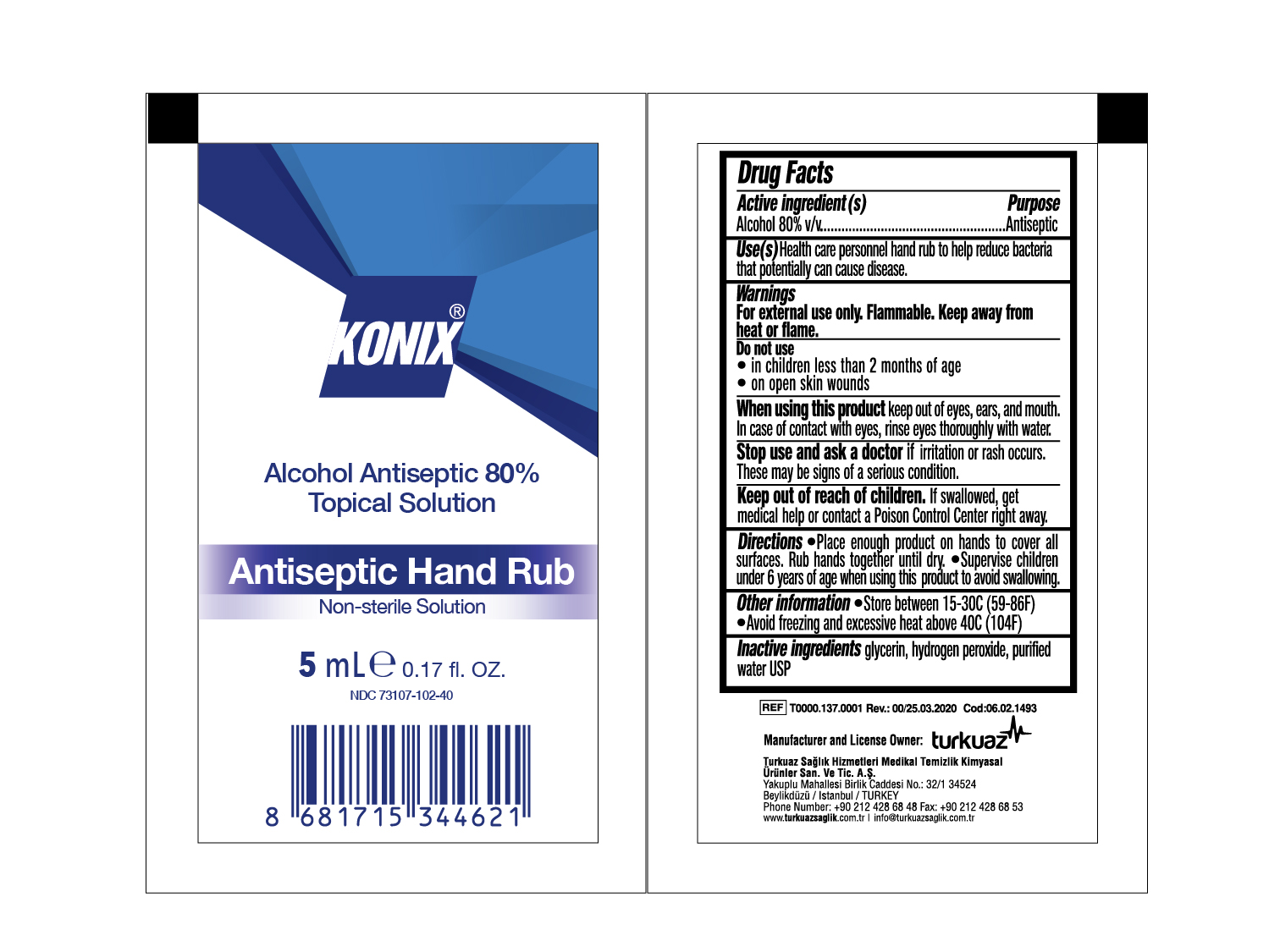 DRUG LABEL: KONIX
NDC: 73107-102 | Form: SOLUTION
Manufacturer: Turkuaz Saglik Hizmetleri Medikal Temizlik Kimyasal Urunler Sanayi ve Tic. AS
Category: otc | Type: HUMAN OTC DRUG LABEL
Date: 20200405

ACTIVE INGREDIENTS: ALCOHOL 80 mL/100 mL
INACTIVE INGREDIENTS: GLYCERIN 1.45 mL/100 mL; HYDROGEN PEROXIDE 0.125 mL/100 mL; WATER 18.425 mL/100 mL

Antiseptic Hand Rub

This is a hand rub manufactured according to the Temporary Policy for Preparation of Certain Alcohol-Based Hand Rub Products During the Public Health Emergency (CoViD-19); Guidance for Industry.

The hand rub is manufactured using only the following United States Pharmacopoeia (USP) grade ingredients in the preparation of the product (percentage in final product formulation) consistent with World Health Organization (WHO) recommendations:

1. Alcohol (ethanol) (USP or Food Chemical Codex (FCC) grade) (80%, volume/volume (v/v)) in an aqueous solution denatured according to Alcohol and Tobacco Tax and Trade Bureau regulations in 27 CFR part 20.
2. Glycerol (1.45% v/v).
3. Hydrogen peroxide (0.125% v/v).
4. Sterile distilled water or boiled cold water.

The firm does not add other active or inactive ingredients. Different or additional ingredients may impact the quality and potency of the product.

Active Ingredient(s)

Alcohol 80% v/v. Purpose: Antiseptic

Purpose

Antiseptic, Hand Rub

Use

Health care personnel hand rub to help reduce bacteria that potentially can cause disease.

Warnings

For external use only. Flammable. Keep away from heat or flame

Do not use

- in children less than 2 months of age
- on open skin wounds

When using this product keep out of eyes, ears, and mouth. In case of contact with eyes, rinse eyes thoroughly with water.
Stop use and ask a doctor if irritation or rash occurs. These may be signs of a serious condition.
Keep out of reach of children. If swallowed, get medical help or contact a Poison Control Center right away.

Stop use and ask a doctor if irritation or rash occurs. These may be signs of a serious condition.

Keep out of reach of children. If swallowed, get medical help or contact a Poison Control Center right away.

Directions

- Place enough product on hands to cover all surfaces. Rub hands together until dry.
- Supervise children under 6 years of age when using this product to avoid swallowing.

Other information

- Store between 15-30C (59-86F)
- Avoid freezing and excessive heat above 40C (104F)

Inactive ingredients

glycerin, hydrogen peroxide, purified water USP

Alcohol Antiseptic 80% Topical SolutionAntiseptic Hand RubNon-sterile Solution

5 ml 0.17fl.OZ NDC: 73107-102-40

PACKAGE LABEL

30 ml 1fl.OZ NDC: 73107-102-30

PACKAGE LABEL

50 ml 1.7fl.OZ NDC: 73107-102-31

PACKAGE LABEL

85 ml 2.8fl.OZ NDC: 73107-102-32

PACKAGE LABEL

100 ml 3.4fl.OZ NDC: 73107-102-33

PACKAGE LABEL

150 ml 5fl.OZ NDC: 73107-102-34

PACKAGE LABEL

200 ml 6.7fl.OZ NDC: 73107-102-35

PACKAGE LABEL

250 ml 8.5fl.OZ NDC: 73107-102-36

PACKAGE LABEL

500 ml 16.9fl.OZ NDC: 73107-102-37

PACKAGE LABEL

1000 ml 33.8fl.OZ NDC: 73107-102-36

PACKAGE LABEL

5000 ml 169fl.OZ NDC: 73107-102-39